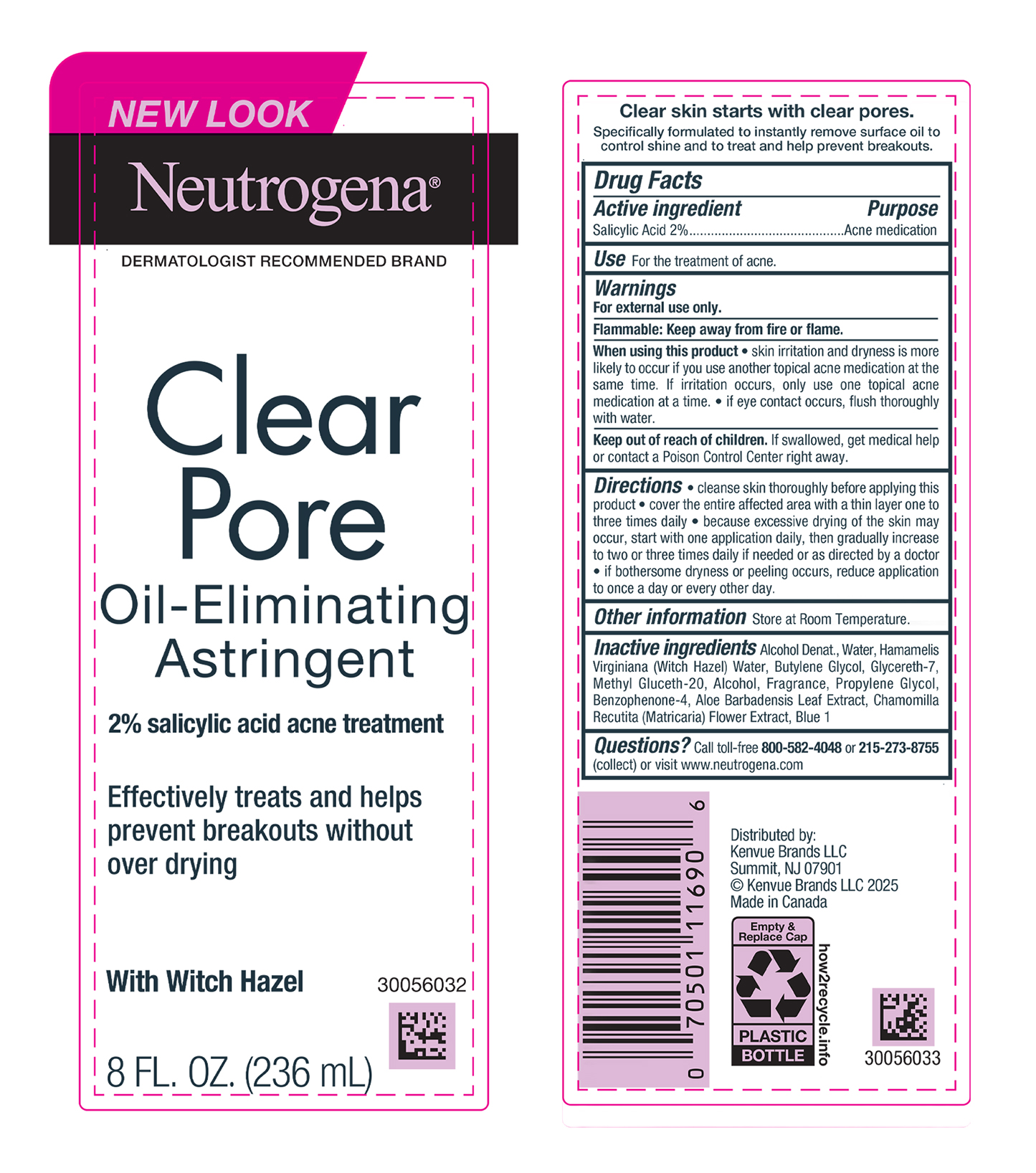 DRUG LABEL: Neutrogena Clear Pore Oil-Eliminating Astringent
NDC: 69968-0028 | Form: LIQUID
Manufacturer: Kenvue Brands LLC
Category: otc | Type: HUMAN OTC DRUG LABEL
Date: 20250409

ACTIVE INGREDIENTS: SALICYLIC ACID 20 mg/1 mL
INACTIVE INGREDIENTS: ALCOHOL; WATER; HAMAMELIS VIRGINIANA TOP WATER; BUTYLENE GLYCOL; GLYCERETH-7; METHYL GLUCETH-20; PROPYLENE GLYCOL; SULISOBENZONE; ALOE VERA LEAF; CHAMOMILE; FD&C BLUE NO. 1

Neutrogena® Clear Pore Oil-Eliminating Astringent

Drug Facts

Active ingredient

Salicylic Acid 2%

Purpose

Acne Medication

Use

For the treatment of acne.

Warnings

For external use only.

Flammable: Keep away from fire or flame.

When using this product

- skin irritation and dryness is more likely to occur if you use another topical acne medication at the same time. If irritation occurs, only use one topical acne medication at a time.
- if eye contact occurs, flush thoroughly with water.

Keep out of reach of children. If swallowed, get medical help or contact a Poison Control Center right away.

directions

- cleanse skin thoroughly before applying this product
- cover the entire affected area with a thin layer one to three times daily
- because excessive drying of the skin may occur, start with one application daily, then gradually increase to two or three times daily if needed or as directed by a doctor
- if bothersome dryness or peeling occurs, reduce application to once a day or every other day.

Other information

Store at Room Temperature

Inactive ingredients

Alcohol Denat., Water, Hamamelis Virginiana (Witch Hazel) Water, Butylene Glycol, Glycereth-7, Methyl Gluceth-20, Alcohol, Fragrance, Propylene Glycol, Benzophenone-4, Aloe Barbadensis Leaf Extract, Chamomilla Recutita (Matricaria) Flower Extract, Blue 1

Questions?

Call toll-free 800-582-4048 or 215-273-8755 (collect) or visit www.neutogena.com

Distributed by:
Kenvue Brands LLC
Summit, NJ 07901

PRINCIPAL DISPLAY PANEL - 236 mL Bottle Label

NEW LOOK

Neutrogena®

DERMATOLOGIST RECOMMENDED BRAND

Clear
Pore
Oil-Eliminating
Astringent

2% salicylic acid acne treatment

Effectively treats and helps

prevent breakouts without

over drying

With Witch Hazel

8 FL. OZ. (236 mL)